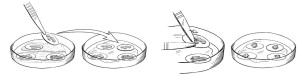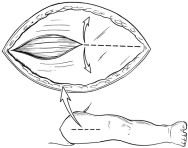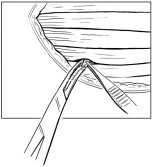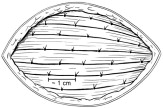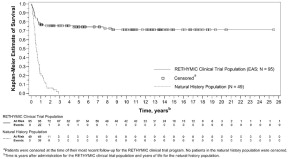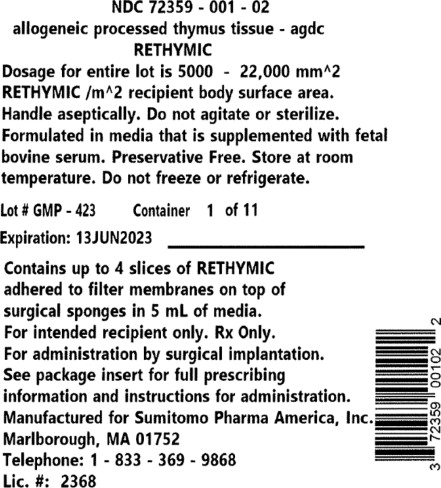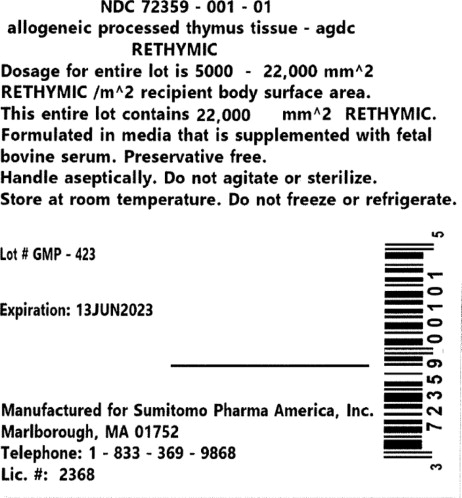 DRUG LABEL: RETHYMIC
NDC: 72359-001 | Form: IMPLANT
Manufacturer: Sumitomo Pharma America, Inc.
Category: prescription | Type: HUMAN PRESCRIPTION DRUG LABEL
Date: 20251031

ACTIVE INGREDIENTS: ALLOGENEIC THYMOCYTE-DEPLETED THYMUS TISSUE-AGDC 22000 mm/1 1
INACTIVE INGREDIENTS: GELATIN PORCINE SKIN, FORMALIN TREATED; ABSORBABLE GELATIN SPONGE; FETAL SERUM, BOVINE

HIGHLIGHTS OF PRESCRIBING INFORMATION

These highlights do not include all the information needed to use RETHYMIC safely and effectively. See full prescribing information for RETHYMIC.
RETHYMIC (Allogeneic processed thymus tissue–agdc)
For surgical implantation
Initial U.S. Approval: 2021

1 INDICATIONS AND USAGE

RETHYMIC is indicated for immune reconstitution in pediatric patients with congenital athymia. (1)

Limitations of Use:

- RETHYMIC is not indicated for the treatment of patients with severe combined immunodeficiency (SCID).

2 DOSAGE AND ADMINISTRATION

RETHYMIC is administered by a surgical procedure. The recommended dose range is 5,000 to 22,000 mm^2 of RETHYMIC/m^2 recipient body surface area (BSA). (2) Immunosuppressive therapy is recommended for patients receiving RETHYMIC based on disease phenotype and PHA levels. (14)

3 DOSAGE FORMS AND STRENGTHS

RETHYMIC consists of yellow to brown slices of processed tissue with varying thickness and shape. The dosage is determined by the surface area of the RETHYMIC slices and recipient BSA. (3)

4 CONTRAINDICATIONS

None.

5 WARNINGS AND PRECAUTIONS

- Immune reconstitution sufficient to protect from infection is unlikely to develop prior to 6 to 12 months after treatment with RETHYMIC. Given the immunocompromised condition of athymic patients, infection control measures should be followed until the development of thymic function can be established. (5.1)
- Monitor and treat patients at risk for the development of graft versus host disease (GVHD). (5.2)
- Monitor for the development of autoimmune disorders, including complete blood counts with differential, liver enzymes, serum creatinine, urinalysis, and thyroid function. (5.3)
- Pre-existing renal impairment is a risk factor for death. (5.4)
- Pre-existing cytomegalovirus infection may result in death prior to the development of thymic function. (5.5)
- Monitor for the development of lymphoproliferative disorder (blood cancer). (5.6)
- Transmission of infectious diseases may occur because RETHYMIC is derived from human tissue. (5.7)
- Immunizations should not be administered in patients who have received RETHYMIC until immune-function criteria have been met. (5.8)
- Patients should be tested for anti-HLA antibodies prior to treatment. (5.9)

6 ADVERSE REACTIONS

The most common (>10%) adverse events related to RETHYMIC included: hypertension (high blood pressure, 19%), cytokine release syndrome (18%), rash (15%), hypomagnesemia (low magnesium, 16%), renal impairment / failure (decrease of kidney function, 12%), thrombocytopenia (low platelets, 12%), and graft versus host disease, (10%). (6.1)

To report SUSPECTED ADVERSE REACTIONS, contact Sumitomo Pharma America at 833-369-9868 or FDA at 1-800-FDA-1088 or https://www.fda.gov/safety/medwatch-fda-safety-information-and-adverse-event-reporting-program.

FULL PRESCRIBING INFORMATION

1 INDICATIONS AND USAGE

RETHYMIC® is indicated for immune reconstitution in pediatric patients with congenital athymia.

Limitations of Use

- RETHYMIC is not indicated for the treatment of patients with severe combined immunodeficiency (SCID).

2 DOSAGE AND ADMINISTRATION

2.1 Dosage

RETHYMIC is administered by a surgical procedure. The dosage is determined by the total surface area of the RETHYMIC slices and recipient body surface area (BSA). A RETHYMIC slice is defined as the contents on a single filter membrane; the RETHYMIC slices are variable in size and shape. The recommended dose range is 5,000 to 22,000 mm^2 of RETHYMIC surface area/m^2 recipient BSA. The manufacturer calculates the dose in advance for the specific patient; the amount of product provided is adjusted at the manufacturing facility to ensure the maximum dose for the patient cannot be exceeded. Up to 42 cultured RETHYMIC slices will be provided for each patient. At the time of surgery, the manufacturing personnel communicate to the surgical team the portion of the product that represents the minimum dose. Patients with evidence of maternal engraftment or an elevated response to phytohemagglutinin (PHA) should receive RETHYMIC with immunosuppressive medications (Table 2).

2.2 Administration Instructions

Surgical implantation of RETHYMIC should be done by a qualified surgical team in a single surgical session at a qualified hospital. RETHYMIC should be implanted in the quadriceps muscle in accordance with the instructions provided below. Implantation of RETHYMIC into the quadriceps requires a healthy bed of muscle tissue.

Preparation for the Implantation Procedure:

1. Operating room culture dishes (sterile 100 mm tissue culture dishes) and saline for injection are supplied by the operating room; a sufficient supply of operating room culture dishes and saline must be provided by the hospital for use in the implantation procedure.
2. The product is delivered to the operating room by manufacturing personnel. The recommended dose is determined based on the patient's BSA. The manufacturer calculates the dose in advance for the specific patient. Manufacturing personnel and the operating room staff confirm that the lot delivered is for the intended recipient.
3. Manufacturing personnel communicate to the surgical team the minimum number of RETHYMIC slices to be implanted to achieve the minimum dose. The product expiration date and time for the entire lot is labeled on each polystyrene dish (drug product dish).
4. Always handle RETHYMIC slices aseptically. Do not use if there is evidence of contamination.
5. Outside the sterile field, manufacturing personnel unpack RETHYMIC from the shipping box. One drug product dish at a time is removed from the drug product box and shipping box. Manufacturing personnel inspect the drug product box and each drug product dish for signs of contamination, damage, spills, or leakage. If damage to the drug product dishes, leaks, spillage or evidence of contamination is noted, manufacturing personnel will notify the surgical team that the lot cannot be implanted.
6. When the surgical team is ready, manufacturing personnel and surgical staff begin the transfer of drug product to the sterile operative field. Manufacturing personnel carry one drug product dish, which contains up to 4 RETHYMIC slices on up to 2 surgical sponges, with each RETHYMIC slice on a filter membrane, to the surgical staff near the sterile field. Manufacturing personnel open the drug product dish to expose the RETHYMIC slices.
7. The surgical staff team member uses a pair of forceps to remove individual RETHYMIC slices with their filter membranes from the drug product dish (Figure 1). The surgical team member places each RETHYMIC slice with its filter membrane into a sterile 100 mm tissue culture dish ("operating room culture dish") containing approximately 2 mL preservative-free saline that resides in the sterile field on the instrument table. This is repeated to transfer all RETHYMIC slices from the first drug product dish into a sterile operating room culture dish. After the first set of RETHYMIC slices has been prepared for surgical implantation and provided to the surgeon, another drug product dish with RETHYMIC slices is passed to the surgical staff member for removal from their filter membranes as described above.
8. Using 2 pairs of sterile forceps, the surgical staff team member should use one pair of forceps to hold the filter in place while using the other forceps to scrape and loosen the RETHYMIC slice from the filter membrane (Figure 1). Then, while using one pair of forceps to hold the filter in place, the surgical staff team member uses the other forceps to lift the RETHYMIC slice away from the filter membrane by pulling the tissue up. The surgical staff team member places each RETHYMIC slice separately into the saline-containing operating room culture dish in the sterile field on top of its original filter membrane. The RETHYMIC slice will change from a flatter slice to a condensed, lumpy shape at this stage of the procedure. The surgeon then implants the first set of RETHYMIC slices. The surgical team staff member should process the next set of up to 4 RETHYMIC slices from the next drug product dish into a second operating room culture dish in the same manner while the surgeon continues implanting the first set of up to 4 slices. When the surgeon finishes implanting the first set of RETHYMIC slices, the surgical staff team member transfers and prepares the next operating room culture dish on the surgical field. Continue this cycle until all the desired tissue is transferred during the implantation procedure.

Figure 1: Preparing for the Implantation Procedure

Figure 1: Within the sterile field, forceps are used to move individual RETHYMIC slices with their filter membranes from the drug product dish to the operating room culture dish (left images). A pair of forceps is used to gently scrape and lift the RETHYMIC slice off the filter membrane in the operating room culture dish in preparation for easy removal prior to implantation (right images).

Implantation of RETHYMIC:

- After induction of general anesthesia, a cranial-caudal skin incision (typically ~5 cm in length; Figure 2) should be made over the anterior thigh compartment. The size of the incision and the use of one or both legs for the implantation procedure is determined by the size of the patient, his/her muscle mass, and the amount of tissue to be implanted. If all or nearly all of the tissue can be implanted in one leg, then only one leg should be used.

Figure 2: Surgical Incision and Opening of Fascia

- Open fascia to expose the anterior compartment muscles (Figure 2).
- Create a pocket in between the muscle fibers using a tonsil clamp or similar instrument. Each pocket should be made along the natural furrows throughout the quadriceps muscle group.
- Individual RETHYMIC slices should be implanted approximately 1 cm in depth and approximately 1 cm apart into the pockets between the muscle fibers in the quadriceps muscle (Figure 3).

Figure 3: Implant Individual RETHYMIC Slices

- A large or thick RETHYMIC slice may be cut in half, at the surgeon's discretion, to ensure the slice is surrounded by muscle tissue once implanted. Implant as many RETHYMIC slices as possible within the recommended dose range of 5,000 to 22,000 mm^2 of processed thymus tissue/m^2 recipient BSA. During the procedure, the surgeon uses their judgment to balance the benefit of implanting additional RETHYMIC slices against the risk(s) that may be associated with implantation into limited muscle mass, number of implantations sites and other patient considerations.
- Once each RETHYMIC slice has been implanted, it should be fully covered by muscle tissue. Then a single absorbable suture should be used to close the pocket where the RETHYMIC slice was implanted (Figure 4).

Figure 4: Close the Site of Implantation

- Once the intended dose has been implanted, confirm hemostasis. Close the skin incision with 2 layers of absorbable sutures and apply a standard dressing, such as wound closure strips or skin glue. Leave the fascia open to allow room for muscle compartment swelling. An occlusive dressing may be used to prevent contamination.

3 DOSAGE FORMS AND STRENGTHS

RETHYMIC consists of yellow to brown slices of processed thymus tissue with varying thickness and shape. Each drug product dish contains up to 4 RETHYMIC slices that adhere to circular filter membranes on top of surgical sponges in 5 mL of medium. The RETHYMIC slices are variable in size and shape; a RETHYMIC slice is defined as the contents of a single filter membrane. The dosage is based on the total surface area of the RETHYMIC slices, and the amount administered is calculated based on recipient BSA. The surgeon should implant as many RETHYMIC slices as possible within the recommended dose range of 5,000 to 22,000 mm^2 of RETHYMIC/m^2 recipient BSA. The manufacturer calculates the dose in advance for the specific patient; the amount of product provided is adjusted at the manufacturing facility to ensure the maximum dose for the patient cannot be exceeded. Up to 42 RETHYMIC slices will be provided for each patient. At the time of surgery, the manufacturing personnel will inform the surgical team of the portion of the product that represents the minimum dose.

4 CONTRAINDICATIONS

None.

5 WARNINGS AND PRECAUTIONS

5.1 Infection Control and Immunoprophylaxis

Immune reconstitution sufficient to protect from infection is unlikely to develop prior to 6-12 months after treatment with RETHYMIC. Given the immunocompromised condition of athymic patients, follow infection control measures until the development of thymic function is established as measured through flow cytometry. This should include counseling patients and their caregivers on good handwashing practices and minimizing exposure to visitors. Monitor patients closely for signs of infection, including fever. If a fever develops, assess the patient by blood and other cultures and treat with antimicrobials as clinically indicated.

Patients should be maintained on immunoglobulin replacement therapy until all of the following criteria are met:

- No longer on immunosuppression (at least 10% of CD3^+ T cells are naïve in phenotype).
- At least 9 months post-treatment.
- Phytohemagglutinin (PHA) response within normal limits.
- Normal serum IgA is also desirable but not required.

Two months after stopping immunoglobulin replacement therapy, the IgG trough level should be checked.

- If the IgG trough level is in the normal range for age, the patient can remain off of immunoglobulin replacement.
- If the IgG trough level is lower than the normal range for age, immunoglobulin replacement therapy should be restarted and continued for a year before being retested using the above guidelines.

Prior to and after treatment with RETHYMIC, patients should be maintained on Pneumocystis jiroveci pneumonia prophylaxis until all of the following criteria are met:

- No longer on immunosuppression (at least 10% of CD3+ T cells are naïve in phenotype).
- At least 9 months post-treatment.
- PHA response within normal limits.
- CD4+ T cell count > 200 cells/mm^3.

5.2 Graft versus Host Disease

In clinical studies with RETHYMIC, GVHD occurred in 11 (10%) RETHYMIC-treated patients of whom 6 (55%) died. RETHYMIC may cause or exacerbate pre-existing GVHD. Seven patients (7%) experienced autologous GVHD, 3 patients (3%) experienced GVHD due to maternal cells and 1 patient (1%) experienced GVHD due to cells from a prior hematopoietic cell transplant (HCT). Risk factors for GVHD include atypical complete DiGeorge anomaly phenotype, prior HCT and maternal engraftment. GVHD may manifest as fever, rash, lymphadenopathy, elevated bilirubin and liver enzymes, enteritis, and/or diarrhea. Patients with elevated baseline T cell proliferative response to PHA > 5,000 cpm or > 20-fold over background should receive immunosuppressive therapies to decrease the risk of GVHD (Table 2 and Table 3). Development of GVHD symptoms should be closely monitored and promptly treated.

5.3 Autoimmune Disorders

Thirty-seven patients (35%) in the RETHYMIC clinical program experienced autoimmune-related adverse reactions. These events included: thrombocytopenia (including idiopathic thrombocytopenic purpura) in 13 patients (12%), neutropenia in 9 patients (9%), proteinuria in 7 patients (7%), hemolytic anemia in 7 patients (7%), alopecia in 4 patients (4%), hypothyroidism in 2 patients (2%), autoimmune hepatitis in 2 patients (2%), and autoimmune arthritis (juvenile idiopathic and psoriatic arthritis) in 2 patients (2%). One patient (1%) each experienced transverse myelitis, albinism, hyperthyroidism, and ovarian failure. The onset of autoimmune related events ranged from the three days before the surgical implantation procedure until 16 years post-treatment. Most events occurred within the first year after treatment.

Monitor complete blood counts with differential weekly for the first 2 months post-treatment and then monthly through 12 months post-treatment. Liver enzymes including aspartate aminotransferase and alanine aminotransferase, serum creatinine levels, and urinalysis should be performed monthly for 3 months and then every 3 months through 12 months post-treatment. Thyroid function studies should be performed prior to treatment and then at 6 months and 12 months post-treatment. After 12 months, testing should be performed annually.

5.4 Renal Impairment

Ten patients with renal impairment (elevated serum creatinine at baseline) were treated in studies with RETHYMIC. Five of these patients died within 1 year and a sixth patient died 3 years after treatment with RETHYMIC. Renal impairment at baseline is considered a risk factor for death.

5.5 Cytomegalovirus Infection

In clinical studies with RETHYMIC, 4 out of 4 patients with preexisting CMV infection prior to treatment with RETHYMIC died. The benefits/risks of treatment should be considered prior to treating patients with pre-existing CMV infection.

5.6 Malignancy

Because of the underlying immune deficiency, patients who receive RETHYMIC may be at risk of developing post-treatment lymphoproliferative disorder (blood cancer). The infant tissue donor is screened for Epstein-Barr virus (EBV) and cytomegalovirus (CMV), but patients should be tested for EBV and CMV using PCR prior to and 3 months following treatment with RETHYMIC, or after any exposure to or suspected infection with CMV or EBV.

5.7 Transmission of Serious Infections and Transmissible Infectious Diseases

Transmission of infectious disease may occur because RETHYMIC is derived from human tissue. Disease may be caused by known or unknown infectious agents. Donors are screened for increased risk of infection with human immunodeficiency virus (HIV), human T-cell lymphotropic virus (HTLV), hepatitis B virus (HBV), hepatitis C virus (HCV), Treponema pallidum, Trypanosoma cruzi, West Nile virus (WNV), transmissible spongiform encephalopathy (TSE) agents, vaccinia. Donors are also screened for clinical evidence of sepsis, and communicable disease risks associated with xenotransplantation. Blood samples (from the infant tissue donor or the birth mother, as applicable) are tested for HIV types 1, 2, and O, HTLV types I and II, HBV, HCV, T. pallidum, WNV, and T. cruzi. Blood from the infant tissue donor is also tested for Toxoplasma gondii, Epstein-Barr virus (EBV) and CMV. RETHYMIC is tested for sterility, endotoxin, and mycoplasma. These measures do not eliminate the risk of transmitting these or other infectious diseases and disease agents.

Testing of maternal and infant donor blood is also performed for evidence of donor infection due to cytomegalovirus (CMV).

Product manufacturing includes porcine- and bovine-derived reagents. While all animal-derived reagents are tested for animal viruses, bacteria, fungi, and mycoplasma before use, these measures do not eliminate the risk of transmitting these or other transmissible infectious diseases and disease agents.

Final sterility and mycoplasma test results are not available at the time of use, but manufacturing personnel will communicate any positive results from sterility testing to the physician. Report the occurrence of transmitted infection to Sumitomo Pharma America at 833-369-9868.

5.8 Vaccine Administration

Immunizations should not be administered in patients who have received RETHYMIC until immune-function criteria have been met.

Inactivated vaccines:

Inactivated vaccines may be administered once all of the following criteria are met:

- Immunosuppressive therapies have been discontinued.
- Immunoglobulin (IgG) replacement therapy has been discontinued.
- The total CD4^+ T cell count is > 200 cells/mm^3 and there are more CD4^+ T cells than CD8^+ T cells (CD4^+ > CD8^+).

It is recommended that no more than 2 inactivated vaccines be given per month.

Live Vaccines:

Live virus vaccines should not be administered until patients have met the criteria for inactivated vaccines and received vaccinations with inactivated agents (e.g., tetanus toxoid). No additional vaccines (live or inactivated), except the inactivated influenza vaccine, should be given within 6 months after vaccination with a measles-containing vaccine or within 2 months after the varicella vaccine. Consider verifying response to vaccination with appropriate testing, in particular varicella and measles.

5.9 Anti-HLA Antibodies

All patients should be screened for anti-HLA antibodies prior to receiving RETHYMIC. Patients testing positive for anti-HLA antibodies should receive RETHYMIC from a donor who does not express those HLA alleles.

5.10 HLA Typing

HLA matching is required in patients who have received a prior hematopoietic cell transplantation (HCT) or a solid organ transplant. Patients who have received a prior HCT are at increased risk of developing GVHD after RETHYMIC if the HCT donor did not fully match the recipient. To minimize this risk, HLA matching of RETHYMIC to recipient alleles that were not expressed in the HCT donor is recommended.

6 ADVERSE REACTIONS

The most common adverse reactions (incidence in at least 10% of patients) reported following administration of RETHYMIC were hypertension (high blood pressure), cytokine release syndrome, rash, hypomagnesemia (low magnesium), renal impairment / failure (decrease of kidney function), thrombocytopenia (low platelets), and graft versus host disease.

6.1 Clinical Trials Experience

Because clinical trials are conducted under widely varying conditions, adverse reaction rates observed in the clinical trials of a drug cannot be directly compared to rates in the clinical trials of another drug and may not reflect the rates observed in practice.

The safety data described in this section are derived from 10 prospective, single-center, open-label studies, and include 105 patients who were treated with RETHYMIC in these studies and who had at least one year of follow-up. Table 1 lists the adverse reactions occurring in 105 patients who were treated with RETHYMIC in these studies.

Table 1: Adverse Reactions Occurring in at least 5% of Patients Treated with RETHYMIC During Clinical Studies
System Organ Class Preferred Term | RETHYMIC (N=105) n (%)
Number of Patients with Adverse Reactions [Reactions which occurred in the 2 years after treatment.] | 80 (76)
Hypertension (high blood pressure) | 20 (19)
Cytokine release syndrome [All events (19/19) of cytokine release syndrome occurred in association with ATG-R treatment.] | 19 (18)
Hypomagnesemia (low magnesium) | 17 (16)
Rash [Rash includes rash, granuloma skin, rash papular, urticaria.] | 16 (15)
Renal impairment / failure [Renal impairment / failure includes renal failure and acute kidney injury, proteinuria and blood creatinine increased.] (decrease of kidney function) | 13 (12)
Thrombocytopenia [Thrombocytopenia includes thrombocytopenia and Immune thrombocytopenic purpura.] (low platelets) | 13 (12)
Graft versus host disease [GVHD includes GVHD, GVHD-gut, GVHD-skin, Omenn syndrome.] | 11 (10)
Hemolytic anemia [Hemolytic anemia includes autoimmune hemolytic anemia, Coombs-positive hemolytic anemia, hemolysis, hemolytic anemia.] (low red bloods cells) | 9 (9)
Neutropenia (low white blood cells) | 9 (9)
Respiratory distress [Respiratory distress includes respiratory distress, hypoxia, respiratory failure.] (difficulty breathing) | 8 (8)
Proteinuria (protein in urine) | 7 (7)
Pyrexia (fever) | 6 (6)
Acidosis [Acidosis includes acidosis, renal tubular acidosis and blood bicarbonate decreased.] | 6 (6)
Diarrhea [Diarrhea includes diarrhea and hemorrhagic diarrhea.] | 5 (5)
Seizure [Seizures include infantile spasms, seizures and febrile convulsion.] | 5 (5)

Of the 105 patients, 29 patients died after receiving RETHYMIC, including 23 deaths in the first year (<365 days) after treatment with RETHYMIC. Causes of death in the first year included 13 deaths due to infection or complications due to infection, 5 deaths due to respiratory failure / hypoxia, 3 deaths due to hemorrhage-related events, and 2 deaths due to cardiorespiratory arrest. Of the 6 patients who died more than 1 year after treatment with RETHYMIC, the deaths were considered unrelated to study treatment: 2 died due to respiratory failure and 1 died due to each of the following: cardiopulmonary arrest, intracranial hemorrhage, infection, and unknown cause.

Severe combined immunodeficiency (SCID) Patients

Two patients with SCID were treated in the RETHYMIC clinical program. One patient died two years after receiving RETHYMIC, and the other patient died three years after receiving RETHYMIC.

Patients with Prior hematopoietic cell transplant

Six patients with a prior hematopoietic cell transplant (HCT) were treated in the RETHYMIC clinical program. Two patients died within the first 2 years after receiving RETHYMIC.

7 DRUG INTERACTIONS

No drug interaction studies have been conducted with RETHYMIC. If possible, prolonged use of immunosuppressive therapies, including high-dose corticosteroids, should be avoided.

8 USE IN SPECIFIC POPULATIONS

8.1 Pregnancy

Risk Summary

There are no clinical data with RETHYMIC in pregnant women. No animal reproductive and developmental toxicity studies have been conducted with RETHYMIC. In the U.S. general population, the estimated background risk of major birth defects and miscarriage in clinically recognized pregnancies is 2-4% and 15-20%, respectively.

8.2 Lactation

Risk Summary

There is no information regarding the presence of cellular components of RETHYMIC in human milk, the effect breastfeeding may have on RETHYMIC, the effect of being breastfed from a mother who received RETHYMIC as a child, or the effects of RETHYMIC on milk production. The developmental and health benefits of breastfeeding should be considered along with the mother's clinical need for RETHYMIC and potential adverse effects on the breastfed infant from RETHYMIC.

8.3 Females and Males of Reproductive Potential

No nonclinical or clinical studies were performed to evaluate the effects of RETHYMIC on fertility.

8.4 Pediatric Use

The efficacy and safety of RETHYMIC have been established in pediatric patients with congenital athymia. The efficacy of RETHYMIC has been established in 95 pediatric patients (median age 9 months [range: 33 days to 3 years], including 65 patients age <1 year, 24 patients age 1 to <2 years, and 6 patients age 2 to <3 years at time of treatment) who were treated with RETHYMIC and included in the analysis of efficacy [see Clinical Studies (14)]. The safety of RETHYMIC has been established in 105 pediatric patients (median age 9 months [range: 33 days to 16.9 years] at time of treatment) with congenital athymia who were evaluated for safety following RETHYMIC administration. The safety population included 65 patients age <1 year, 27 patients age 1 to <2 years, 9 patients age 2 to <3 years, 1 patient age 3 to <6 years, and 3 patients age 13 to 17 years at time of treatment. Within the safety population, survival was similar across age groups. Adverse reactions were reported at similar frequencies across the age groups and were generally of similar types and severities.

8.6 Renal Impairment

In the clinical studies with RETHYMIC, 10 of 105 patients had impaired renal function at baseline based on elevated screening creatinine [see Warnings and Precautions (5.4)]. Baseline renal function should be considered when selecting immunosuppressants. Ensure appropriate involvement of a nephrologist in care of patients with renal impairment.

10 OVERDOSAGE

The maximum recommended dose is 22,000 mm^2 of RETHYMIC/m^2 recipient body surface area (BSA). Standard clinical care is recommended for patients receiving a dose > 22,000 mm^2 of RETHYMIC/m^2 recipient BSA. The product, as provided, has been adjusted at the manufacturing facility to not exceed the maximum dose based on the patient body surface area.

During clinical development one patient received a dose higher (23,755 mm^2/m^2) than the maximum recommended dose. This patient developed enteritis. A biopsy showed T cell, B cell, and neutrophil infiltration of the gut which resolved after treatment with immunosuppression, 5 months after treatment with RETHYMIC. The enteritis may have been related to the high dose of RETHYMIC.

11 DESCRIPTION

RETHYMIC consists of yellow to brown slices of allogeneic processed thymus tissue for administration by surgical implantation. Three to 11 drug product containers, with a total of 10 to 42 RETHYMIC slices, are provided for each patient. Each drug product container provides up to 4 RETHYMIC slices of variable size. The total dose, based on the number of slices administered to the patient, is 5,000 to 22,000 mm^2 of RETHYMIC/m^2 recipient BSA.

Thymus tissue is obtained from donors less than or equal to 9 months of age undergoing cardiac surgery. This thymus tissue is aseptically processed and cultured for 12 to 21 days to produce RETHYMIC slices. Each product lot is manufactured from a single unrelated donor and one product lot treats a single patient. The manufacturing process preserves the thymic epithelial cells and tissue structure and depletes most of the donor thymocytes from the tissue. These RETHYMIC slices are then surgically implanted into patients with congenital athymia.

The product manufacture uses reagents derived from animal materials. The surgical sponge used during culturing is porcine-derived. Fetal bovine serum is a component in the culture medium used to culture the thymus slices and RETHYMIC is formulated in media that is supplemented with fetal bovine serum. Therefore, bovine- and porcine-derived proteins will be present in RETHYMIC. These animal-derived reagents are tested for animal viruses, retroviruses, bacteria, fungi, yeast, and mycoplasma before use.

12 CLINICAL PHARMACOLOGY

12.1 Mechanism of Action

RETHYMIC is intended to reconstitute immunity in patients who are athymic. The proposed mechanism of action involves the migration of recipient T cell progenitors from the bone marrow to the implanted RETHYMIC slices, where they develop into naïve immunocompetent recipient T cells. Evidence of thymic function can be observed with the development of naïve T cells in the peripheral blood; this is unlikely to be observed prior to 6-12 months after treatment with RETHYMIC.

12.2 Pharmacodynamics

The pharmacodynamic effects of RETHYMIC are not known.

12.3 Pharmacokinetics

The pharmacokinetic effects of RETHYMIC are not known.

14 CLINICAL STUDIES

The efficacy of RETHYMIC was evaluated in 10 prospective, single-center, open-label studies that enrolled a total of 105 patients, including 95 patients in the primary efficacy analysis. The demographics and baseline characteristics of the patients enrolled in the clinical studies were similar across studies. Across the efficacy population, 59% were male; 70% were White, 22% were Black, 4% were Asian/Pacific Islander; 2% were American Indian/Alaskan Native; and 2% were multi-race. The median (range) age at the time of treatment was 9 months (1-36). The diagnosis of congenital athymia was based on flow cytometry documenting fewer than 50 naïve T cells/mm^3 (CD45RA^+, CD62L^+) in the peripheral blood or less than 5% of total T cells being naïve in phenotype in 91/95 patients (range 0-98 naïve T cells/mm^3). In addition to congenital athymia, patients also had complete DiGeorge syndrome (cDGS; also referred to as complete DiGeorge anomaly (cDGA)) if they also met at least one of the following criteria: congenital heart defect, hypoparathyroidism (or hypocalcemia requiring calcium replacement), 22q11 hemizygosity, 10p13 hemizygosity, CHARGE (coloboma, heart defect, choanal atresia, growth and development retardation, genital hypoplasia, ear defects including deafness) syndrome, or CHD7 mutation. Across the efficacy population, 93 patients (98%) were diagnosed with cDGS, and the most common DiGeorge gene mutations or syndromic associations were Chromosome 22q11.2 deletion (36 patients; 38%) and CHARGE syndrome (23 patients; 24%). There were 35 patients with missing or no identified genetic mutations. Two (2%) patients had FOXN1 deficiency, and 1 patient (1%) had a TBX variant. There were 50 (53%) patients with typical cDGS; these patients had congenital athymia with the absence of a T cell-related rash. There were 42 (44%) patients diagnosed with atypical cDGS; these patients may have had a rash, lymphadenopathy, or oligoclonal T cells. Patients who did not have congenital athymia (e.g. SCID) and patients with prior transplants, including thymus and HCT, were excluded from the efficacy analysis population. The baseline demographics and disease characteristics were similar in the safety population.

Patients with heart surgery anticipated within 4 weeks prior to, or 3 months after, the planned RETHYMIC treatment date, patients with human immunodeficiency virus (HIV) infection, and patients who were not considered good surgical candidates were excluded from study participation.

Patients in the efficacy population received RETHYMIC in a single surgical procedure at a dose of 4,900 to 24,000 mm^2 of RETHYMIC / recipient BSA in m^2. Patients were assigned to receive immunosuppressive therapy prior to and/or after treatment according to their disease phenotype and pre-RETHYMIC PHA response. Table 2 summarizes the criteria used to administer immunosuppression. Table 3 summarizes the specific immunosuppressant dosing used in RETHYMIC clinical studies. No patients were retreated with RETHYMIC.

Table 2: Summary of Treatment Assignment to Immunosuppression During Clinical Studies
Complete DiGeorge Anomaly Phenotype | Phytohemagglutinin (PHA) Response [Values for PHA response are reported from Duke University Medical Center and may not be comparable to values reported at other clinical laboratories. A patient background value (cells without stimulus) of less than 5,000 cpm was required to consider PHA test results valid. A normal control value of > 75,000 cpm was also required during clinical studies.] | Immunosuppression Used During Clinical Studies with RETHYMIC
Typical | < 5,000 cpm or < 20-fold response to PHA over background | None
Typical | ≥ 5,000 cpm and < 50,000 cpm or Evidence of maternal engraftment | - ATG-R - Methylprednisolone
Typical | ≥ 50,000 cpm | - ATG-R - Methylprednisolone - Cyclosporine [If the patient could not tolerate cyclosporine due to adverse events (AEs), then the immunosuppression could have been changed to tacrolimus.]
Atypical | < 40,000 cpm on immunosuppression or < 75,000 cpm when not on immunosuppression | - ATG-R - Methylprednisolone - Cyclosporine
Atypical | ≥ 40,000 cpm on immunosuppression or ≥ 75,000 cpm when not on immunosuppression or Evidence of maternal engraftment | - ATG-R - Methylprednisolone - Cyclosporine - Basiliximab [Basiliximab could have been given 24 hours prior to RETHYMIC administration for activated T cells (> 200 cells/mm 3 or > 50% T cells expressing CD25 +) persisting after ATG-R administration. Post-implantation, if the T cell count was > 2000 cells/mm 3 and > 50% of T cells were expressing CD25 +, a single dose of basiliximab could be given if not previously administered.] - MMF [MMF could have been given if T cells remained elevated 5 days after ATG-R administration. MMF was stopped after 35 days if there was no extensive rash and if the aspartate aminotransferase and alanine aminotransferase were less than 3× the upper limit of normal and if T cells were < 5,000 cells/mm 3. If these criteria were not met, MMF could have been continued for up to 6 months.]
Abbreviations: ATG-R: anti-thymocyte globulin [rabbit] (Thymoglobulin); cpm: counts per minute; MMF: mycophenylate mofetil; PHA: phytohemagglutinin

Table 3: Summary of Immunosuppressant Dosing During Clinical Studies
Immunosuppressant | Dose of Immunosuppressant
ATG-R | - 2 mg/kg IV administered once per day for 3 consecutive days pre-implantation (3 total doses) - Administered over ~12 hrs starting at 0.125 ml/kg/hr into a central line for 1 hr, then 0.25 mL/kg/hr × 1 hr, then 0.35 mg/kg/hr for remainder of the infusion - RETHYMIC implantation occurred within 7 days of last dose of ATG-R - If the implant occurred more than 7 days after the last dose of ATG-R, a T cell count was repeated: - If the T cell count was <50/mm^3, no more ATG-R was administered - If the T cell count was >50/mm^3, ATG-R was repeated at the same schedule and dose as the initial infusion. - Administration was planned for Days -5, -4, and -3 pre-implantation, followed by 2 days of rest prior to implantation.
Methylprednisolone [Additional pre-implantation corticosteroids (methylprednisolone) were used for atypical patients if pre-implantation CD3 + T cell numbers or the absolute lymphocyte count (ALC) was greater than 4,000 cells/mm 3. A starting dose of 1 mg/kg/day was used if the T cell count or ALC was between 4,000 and 10,000 cells/mm 3. A dose of 2 mg/kg/day was used if the T cell count was > 10,000 cells/mm 3.] , [Corticosteroids (methylprednisolone or prednisolone) were initiated as soon as the diagnosis was confirmed in patients with evidence of maternal engraftment or with atypical cDGS and a PHA response of > 40,000 cpm on immunosuppression or > 75,000 cpm when not on immunosuppression. The steroid was weaned as soon as possible when the rash and other symptoms were brought under control.] | - 2 mg/kg IV × 1 dose 4 hrs prior to ATG-R, then 0.5 mg/kg IV every 6 hrs until 24 hrs after the end of the ATG-R dosing
Cyclosporine [Cyclosporine was initiated as soon as the diagnosis was confirmed and at least 7 days prior to ATG-R administration. If the CD3 + T cells fell and remained below 50/mm 3, cyclosporine was weaned to have a cyclosporine trough level of 100 to 150 ng/mL. If the T cell count remained over 50/mm 3, cyclosporine was maintained until the naive T cells were 10% of CD3 + T cells. Cyclosporine was then weaned over 10 weeks. To preserve renal function, the initiation of cyclosporine may have been delayed prior to implantation. Renal function was monitored according to the cyclosporine or tacrolimus prescribing information.] , [A higher target trough concentration of 250 to 300 ng/mL was used in patients with evidence of maternal engraftment or with atypical cDGS and a PHA response of > 40,000 cpm on immunosuppression or > 75,000 cpm when not on immunosuppression.] , [If the patient could not tolerate cyclosporine due to adverse events (AEs), then the immunosuppression could have been changed to tacrolimus (target trough concentration of 7 to 10 ng/mL). In patients with evidence of maternal engraftment or with atypical cDGS and a PHA response of > 40,000 cpm on immunosuppression or > 75,000 cpm when not on immunosuppression, the tacrolimus target trough level was 10 to 15 ng/mL.] | - Target trough level of 180 to 220 ng/mL
Basiliximab | - A single dose of 5 mg/kg IV
MMF | - 15 mg/kg/dose q 8 hrs IV or PO
Alemtuzumab [Premedications given 30 minutes prior to alemtuzumab include methylprednisolone (1 mg/kg IV), acetaminophen (10 mg/kg IV), and diphenhydramine, (0.5 mg/kg IV).] | - 0.25 mg/kg daily, infused over 2 hours × 4 days IV
Abbreviations: ATG-R: anti-thymocyte globulin [rabbit] (Thymoglobulin); IV: intravenous; MMF: mycophenylate mofetil; PO: oral

The Kaplan-Meier estimated survival rates were 77% (95% CI [0.670, 0.841]) at 1 year and 76% (95% CI [0.658, 0.832]) at 2 years. For patients who were alive at 1 year after treatment with RETHYMIC, the survival rate was 94% at a median follow-up of 10.7 years.

Without treatment, congenital athymia is fatal in childhood. In a natural history population observed from 1991 through 2017, 49 patients diagnosed with congenital athymia received supportive care only. The 2-year survival rate was 6%, with all patients dying by 3 years of age. This population included 33 (67%) males. The most common cause of death was infection in 26 (53%) patients. Other common causes (≥10%) included support withdrawn in 7 (14%) patients, respiratory arrest in 5 (10%) patients, and cardiac arrest in 5 (10%) patients.

The Kaplan-Meier estimated survival rates for the RETHYMIC clinical trial population and the natural history population are shown in Figure 5. Four patients with >50 naïve T cells/mm^3 (CD45RA^+, CD62L^+) at time of RETHYMIC administration have been treated; 2 (50%) were alive with follow-up less than 2 years.

Figure 5: Kaplan-Meier Survival by Year (RETHYMIC Efficacy Analysis Population and Natural History Population)

RETHYMIC significantly reduced the number of infections over time. In the first year after treatment with RETHYMIC, the number of patients with an infection event onset 6 to ≤ 12 months after treatment decreased by 38% (from 63 to 39) relative to the number of patients with an infection event onset in the first 6 months post-treatment. A two-year analysis showed a decrease in both the number of patients with an infection event and the mean number of infection events per patient, with an onset in the first 12 months post-treatment as compared to 12 to ≤ 24 months after treatment. There was a mean difference of 2.9 events (p<0.001) per patient.

Naïve CD4^+ and CD8^+ T cells reconstituted over the first year, with a durable increase through Year 2. Median (minimum, maximum) naïve CD4^+ T cells/mm^3 increased from a baseline of 1 (0, 38) to values of 42 (0, 653), 212 (1, 751), and 275 (33, 858) at 6, 12, and 24 months after treatment with RETHYMIC, respectively. Median naïve CD8^+ T cells/mm^3 increased from a baseline of 0 (0, 46) to values of 9 (0, 163), 58 (0, 304), and 86 (6, 275) at 6, 12, and 24 months after treatment with RETHYMIC, respectively. This was accompanied by functional improvements based on T cell proliferative responses to PHA.

16 HOW SUPPLIED/STORAGE AND HANDLING

How Supplied

- RETHYMIC, NDC 72359-001-01, contains a single-dose unit, supplied ready for use as slices of processed thymus tissue, in sterile, polystyrene dishes (drug product dishes). Each drug product dish contains up to 4 RETHYMIC slices, adhered to circular filter membranes on top of surgical sponges in 5 mL of medium containing fetal bovine serum.
- Up to 42 RETHYMIC slices are supplied in a single-dose unit according to the dosage calculated in advance by the manufacturer for the specific patient. The dosage is determined by the total surface area of the RETHYMIC slices and recipient body surface area (BSA). The recommended dose range is 5,000 to 22,000 mm^2 of RETHYMIC surface area/m^2 recipient BSA. At the time of surgery, the manufacturing personnel communicate to the surgical team the portion of the product that represents the minimum dose.
- All drug product dishes are supplied in a polycarbonate container in an insulated shipping box.

Storage and Handling

- Use RETHYMIC prior to the time and date of expiration printed on the polycarbonate container.
- Store RETHYMIC at room temperature in the polycarbonate container in the insulated shipping box until ready for use. Do not refrigerate, freeze, agitate, or sterilize RETHYMIC.
- In the operating room, manufacturing personnel inspect the drug product containers as they are removed from the shipping box. If damage to the drug product dishes, leaks, spillage or evidence of contamination is noted, manufacturing personnel will notify the surgical team that the lot cannot be implanted.
- Match the patient's identity with the patient identifiers on the patient label on the polycarbonate container. Do not remove the drug product containers from the polycarbonate container if the information on the patient label does not match the intended patient.
- Manufacturing personnel record which RETHYMIC slices are used during the surgery. If any RETHYMIC slices are not administered to the patient, manufacturing personnel return this tissue to the manufacturing facility and dispose of this tissue as biohazardous waste in accordance with local requirements. Manufacturing personnel calculate the total dose that was administered to the patient.

17 PATIENT COUNSELING INFORMATION

Advise patients and/or their caregivers that:

- Immune reconstitution sufficient to protect from infection usually develops between 6-12 months after treatment with RETHYMIC, but for some patients elevated naïve T cell numbers are not observed until 2 years after treatment. Strict infection control measures should be observed until the healthcare provider confirms that immune function has been reconstituted through the evaluation of blood using flow cytometry and the criteria for the discontinuation of immunoglobulin replacement therapy and Pneumocystis jiroveci pneumonia prophylaxis have been met. Patients and caregivers should follow good handwashing practices, minimize contact with others, and immediately report signs and symptoms of infection to their healthcare provider [see Warnings and Precautions (5.1)].
- Congenital athymia alters the immune response to vaccines. Instruct patients and/or their caregivers to notify their healthcare professional to evaluate the immune status of RETHYMIC recipients prior to receiving vaccinations [see Warnings and Precautions (5.8)].
- Immunosuppression should be administered in patients with elevated T cell response, maternal engraftment, or oligoclonal T cell expansion and autoreactive T cells manifested by rash, lymphadenopathy and/or diarrhea. Inform patients and/or their caregivers on risks associated with short-term and long-term use of immunosuppression and refer them to review the risks of the specific immunosuppressants prescribed with their physician.
- Congenital athymia is associated with a wide spectrum of genetic anomalies. Instruct patients and/or their caregiver to consult with a clinical geneticist prior to receiving RETHYMIC.

Advise patients and/or their caregivers of the following risks:

- Graft versus Host Disease [see Warnings and Precautions (5.2)]
- Autoimmune Disorders (patient's immune (defense) system mistakenly attacks patient's body) [see Warnings and Precautions (5.3)]
- Renal Impairment (decrease of kidney function) [see Warnings and Precautions (5.4)]
- Cytomegalovirus Infection [see Warnings and Precautions (5.5)]
- Malignancy (Cancer) [see Warnings and Precautions (5.6)]
- Transmission of Serious Infections and Transmissible Infectious Diseases [see Warnings and Precautions (5.7)]

Manufactured for:

Sumitomo Pharma America, Inc.
84 Waterford Drive
Marlborough, MA 01752

PRINCIPAL DISPLAY PANEL - 22,000 mm Container Label

NDC 72359–001–02
allogeneic processed thymus tissue–agdc
RETHYMIC
Dosage for entire lot is 5000 – 22,000 mm^2
RETHYMIC /m^2 recipient body surface area.
Handle aseptically. Do not agitate or sterilize.
Formulated in media that is supplemented with fetal
bovine serum. Preservative Free. Store at room
temperature. Do not freeze or refrigerate.

Lot # GMP–423
Container 1 of 11

Expiration: 13JUN2023

Contains up to 4 slices of RETHYMIC
adhered to filter membranes on top of
surgical sponges in 5 mL of media.
For intended recipient only. Rx Only.
For administration by surgical implantation.
See package insert for full prescribing
information and instructions for administration.
Manufactured for Sumitomo Pharma America, Inc.
Marlborough, MA 01752
Telephone: 1–833–369–9868
Lic. #: 2368

PACKAGE LABEL

PRINCIPAL DISPLAY PANEL - 22,000 mm Container Box Label

NDC 72359–001–01
allogeneic processed thymus tissue–agdc
RETHYMIC

Dosage for entire lot is 5000 – 22,000 mm^2
RETHYMIC /m^2 recipient body surface area.
This entire lot contains 22,000 mm^2 RETHYMIC.
Formulated in media that is supplemented with fetal
bovine serum. Preservative free.
Handle aseptically. Do not agitate or sterilize.
Store at room temperature. Do not freeze or refrigerate.

Lot # GMP–423

Expiration: 13JUN2023

Manufactured for Sumitomo Pharma America, Inc.
Marlborough, MA 01752
Telephone: 1–833–369–9868
Lic. #: 2368